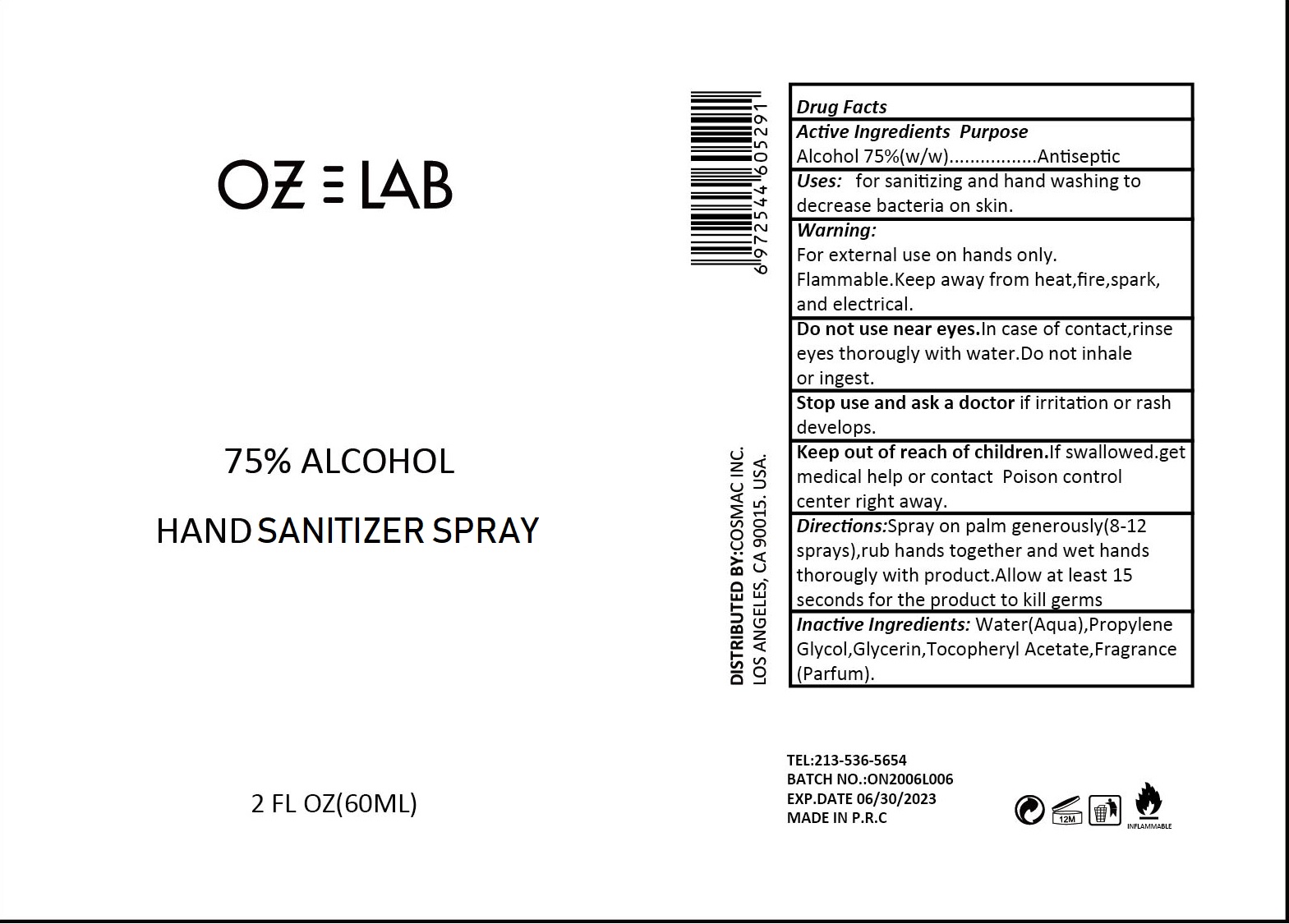 DRUG LABEL: OZLAB Hand Sanitizer
NDC: 75531-004 | Form: SPRAY
Manufacturer: Zhejiang Ounuo Cosmetics Co., Ltd.
Category: otc | Type: HUMAN OTC DRUG LABEL
Date: 20200528

ACTIVE INGREDIENTS: alcohol 75 mL/100 mL
INACTIVE INGREDIENTS: WATER; PROPYLENE GLYCOL; GLYCERIN; .ALPHA.-TOCOPHEROL ACETATE, D-

Drug facts

Active ingredient

Alcohol 75% (w/w)

Purpose - Antiseptic

KEEP OUT OF REACH OF CHILDREN

If swallowed, get medical help or contact a Poison Control Center right away.

INDICATIONS AND USAGE

For sanitizing and hand washing to decrease bacteria on skin

WARNINGS

For external use only: hands
Flammable. Keep away from heat, fire or spark, and electical.

Do not use near eyes. In case of contact, rinse eyes thoroughly with water Do not inhale or ingest.

Stop using and ask a doctor, if irritation or rash develops.

DOSAGE AND ADMINISTRATION

Directions - Spray on palm generously (8-12 spprays), rub hands together and wet hands thoroughly with product. Allow at least 15 seconds for the product to kill germs.

INACTIVE INGREDIENT

Water (aqua), propylene glycol, Glycerin, Tocpheryl Acetate, fragrance (parfum)